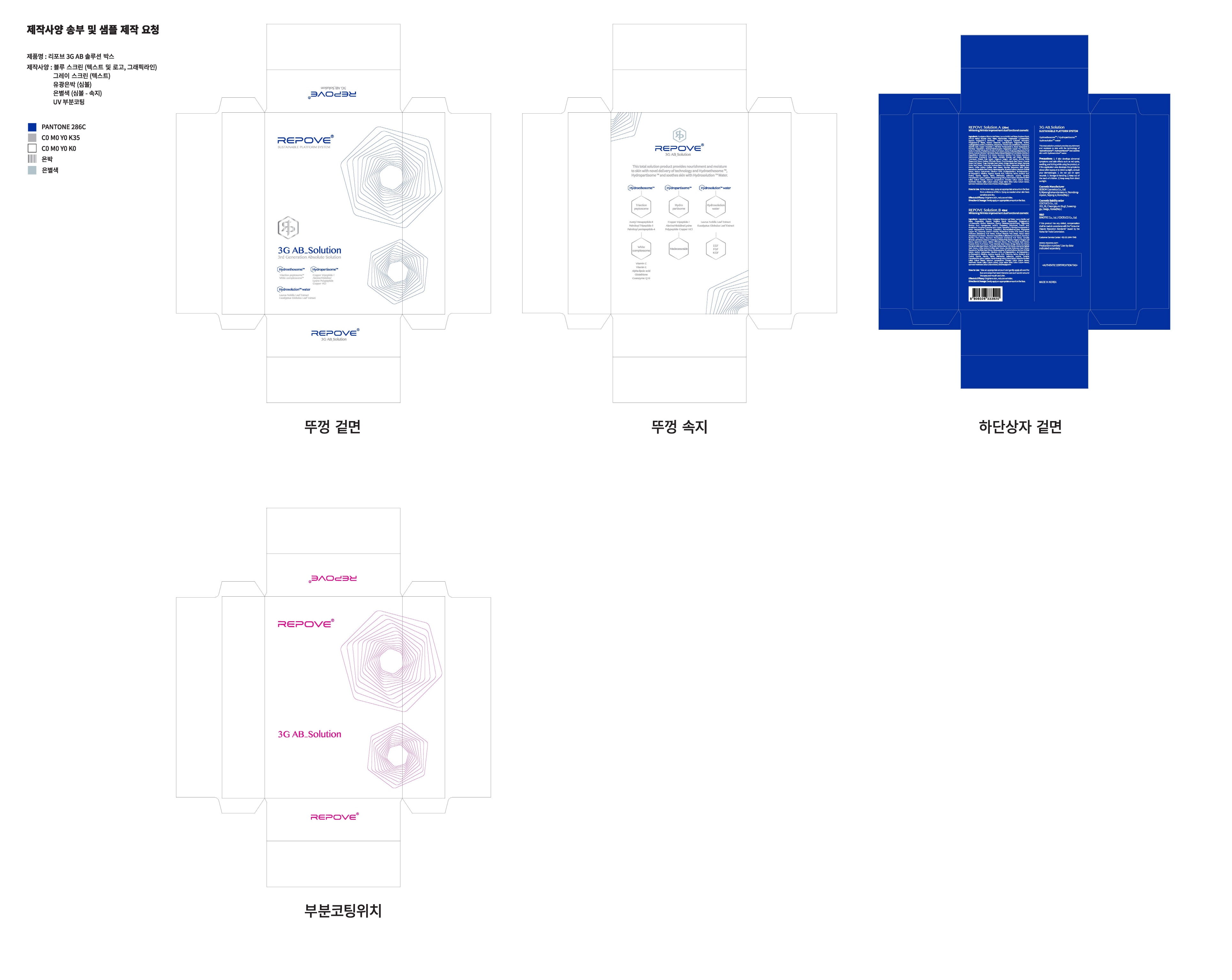 DRUG LABEL: RepoveSolutionB
NDC: 73345-0020 | Form: LIQUID
Manufacturer: Binotec Co., Ltd.
Category: otc | Type: HUMAN OTC DRUG LABEL
Date: 20190924

ACTIVE INGREDIENTS: GLYCERIN 3.6201 g/100 mL
INACTIVE INGREDIENTS: WATER; ADENOSINE

Drug Facts

ACTIVE INGREDIENT

Glycerin

INACTIVE INGREDIENT

Water
Eucalyptus Globulus Leaf Water
Laurus Nobilis Leaf Water
Propanediol
Butylene Glycol
Niacinamide
Polyglycerin-3
1,2-Hexanediol
Alcohol
Adenosine
Glyceryl Distearate
Caprylic/Capric Triglyceride
Xanthan Gum
Hydrogenated lecithin
Cholesterol
Ubiquinone
Thioctic Acid
Glutathione
Tocopherol
Ascorbic Acid
Copper Tripeptide-1
Palmitoyl Pentapeptide-4
Acetyl Hexapeptide-8
Palmitoyl Tripeptide-5
Alanine/Histidine/Lysine Polypeptide Copper HCl
Carbomer
Sodium Chloride
lanthus Emblica Fruit Extract
Rubus Fruticosus (Blackberry) Fruit Extract
Euterpe Oleracea Fruit Extract
Rubus Idaeus (Raspberry) Fruit Extract
ium Angustifolium (Blueberry) Fruit Extract
Vaccinium Myrtillus Fruit Extract
Vaccinium Macrocarpon (Cranberry) Fruit Extract
Camellia Sinensis Leaf Extract
Solanum Tuberosum (Potato) Pulp Extract
Origanum Vulgare Leaf Extract
Mentha Viridis (Spearmint) Extract
Melissa Officinalis Extract
Pinus Koraiensis Seed Extract
Hovenia Dulcis Fruit Extract
Thuja Orientalis Seed Extract
Ginkgo Biloba Nut Extract
Myrciaria Dubia Seed Extract
Terminalia Ferdinandiana Fruit Extract
Adansonia Digitata Seed Extract
Coffea Arabica (Coffee) Seed Extract
Aleurites Moluccana Seed Extract
Macadamia Ternifolia Seed Extract
Madecassoside
Dimethyl Sulfone
Morinda Citrifolia Extract
Sodium Hyaluronate
Disodium EDTA
sh-Oligopeptide-1
sh-Polypeptide-1
sh-Polypeptide-3
Histidine
Arginine
Aspartic Acid
Threonine
Serine
Glutamic Acid
Proline
Glycine
Alanine
Valine
Methionine
Isoleucine
Leucine
Tyrosine
Phenylalanine
Lysine
Cysteine
Panax Ginseng Callus Culture Extract
Nelumbo Nucifera Callus Culture Extract
Solanum Lycopersicum (Tomato) Callus Culture Extract
Neofinetia Falcata Callus Culture Extract
Oryza Sativa (Rice) Callus Culture Extract
Ipomoea Hederacea Callus Culture Extract
Ethylhexylglycerin

PURPOSE

Skin protectant

keep out of reach of the children

INDICATIONS AND USAGE

Apply it proper amount to the skin.

DOSAGE AND ADMINISTRATION

for external use only

WARNINGS

If skin shows the following reactions while using 3G AB_Solution, reduce the amount of use drastically or discontinue use.

1. If itching continues for 7-10 days

2. If skin experiences a burning sensation or becomes reddish (dry skin type, particularly extremely dry skin)

3. If dead skin cells are generated drastically

* If you are receiving skin treatment due to skin diseases consult your doctor before use.